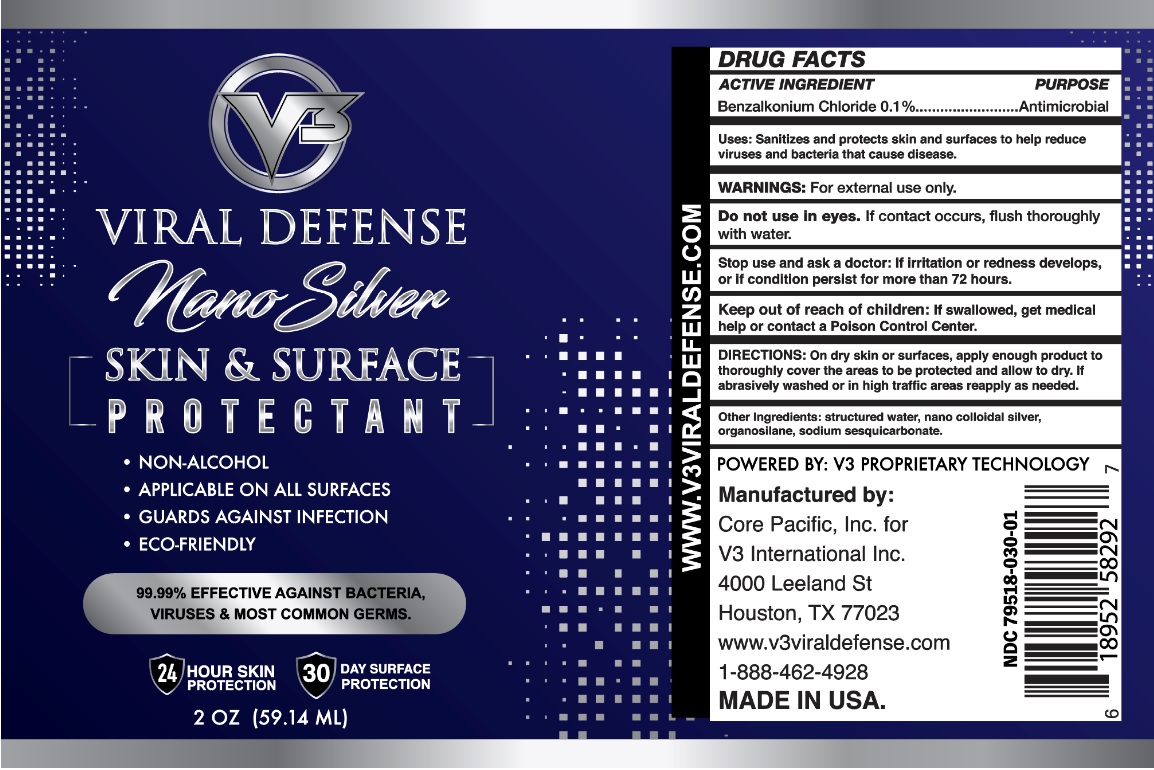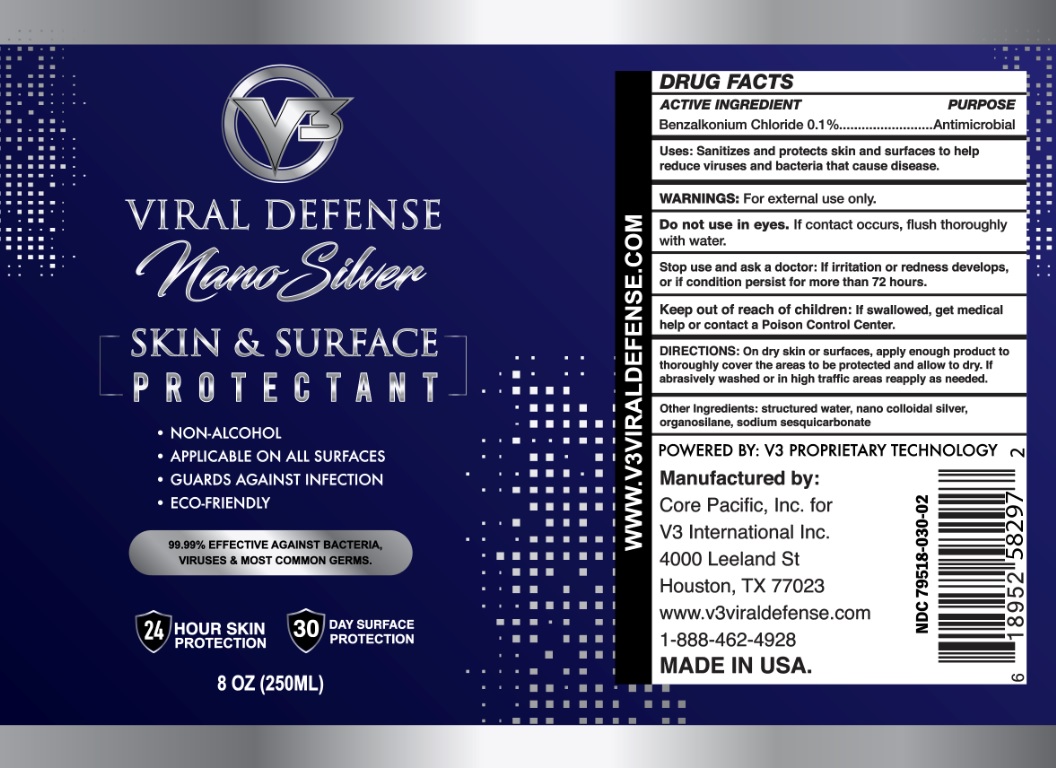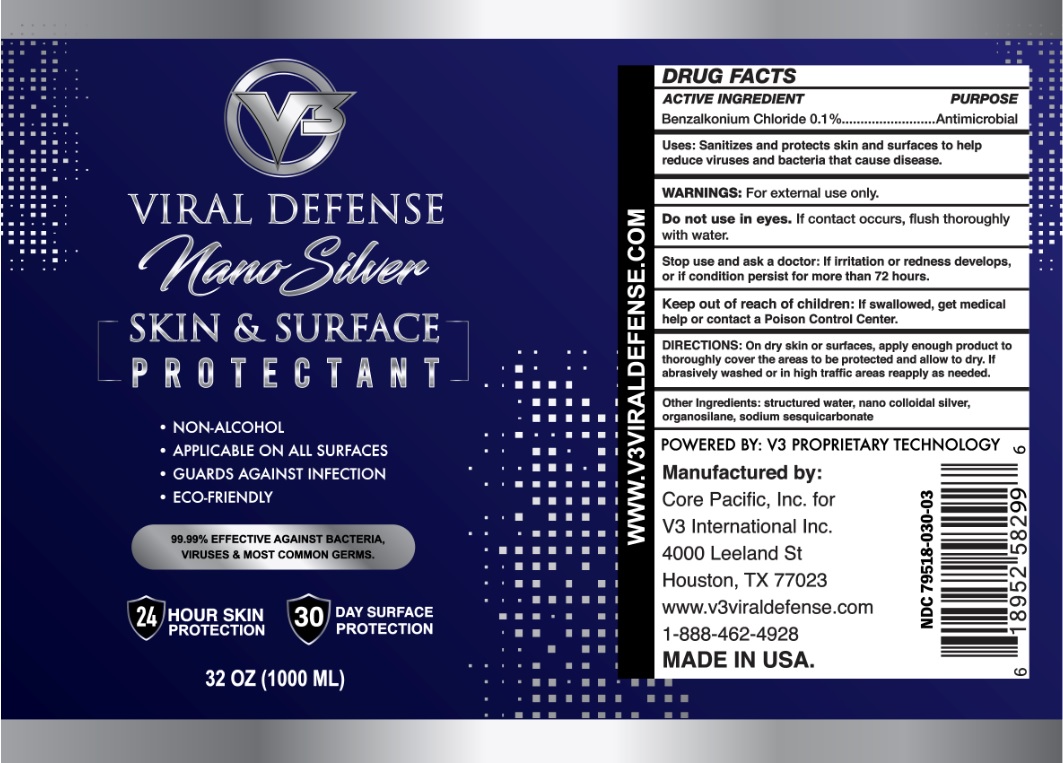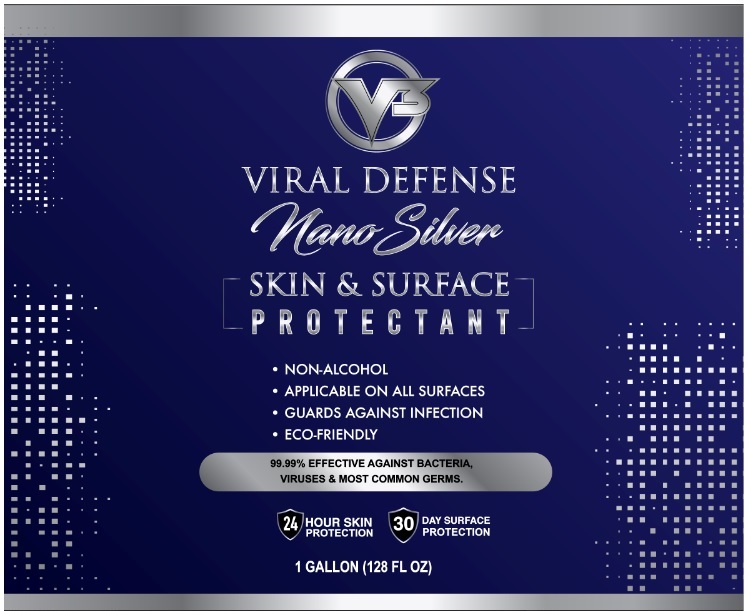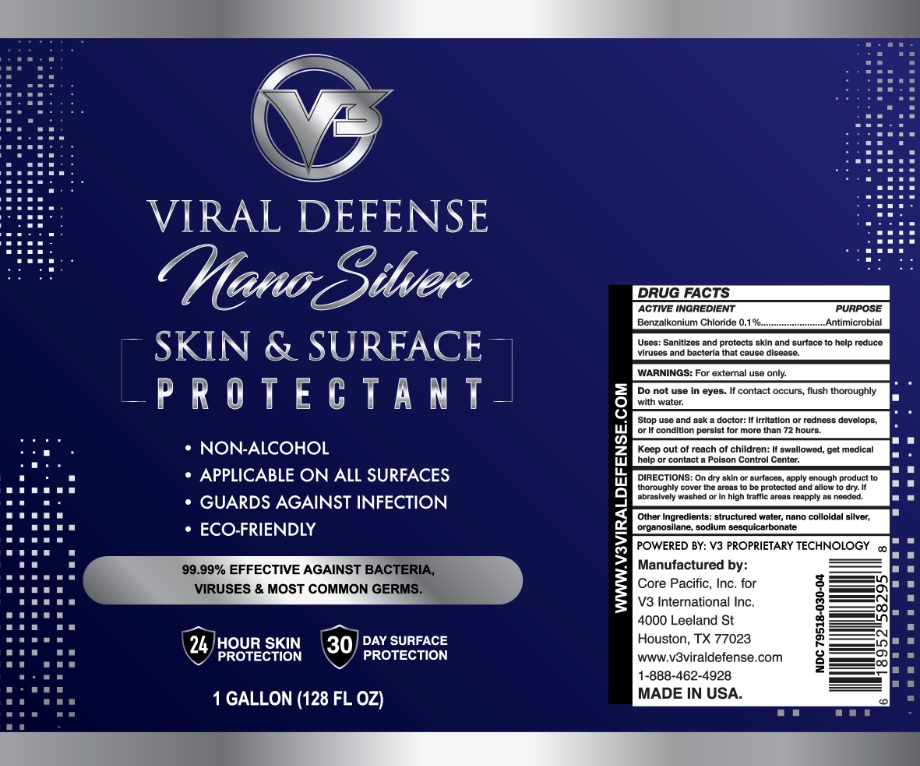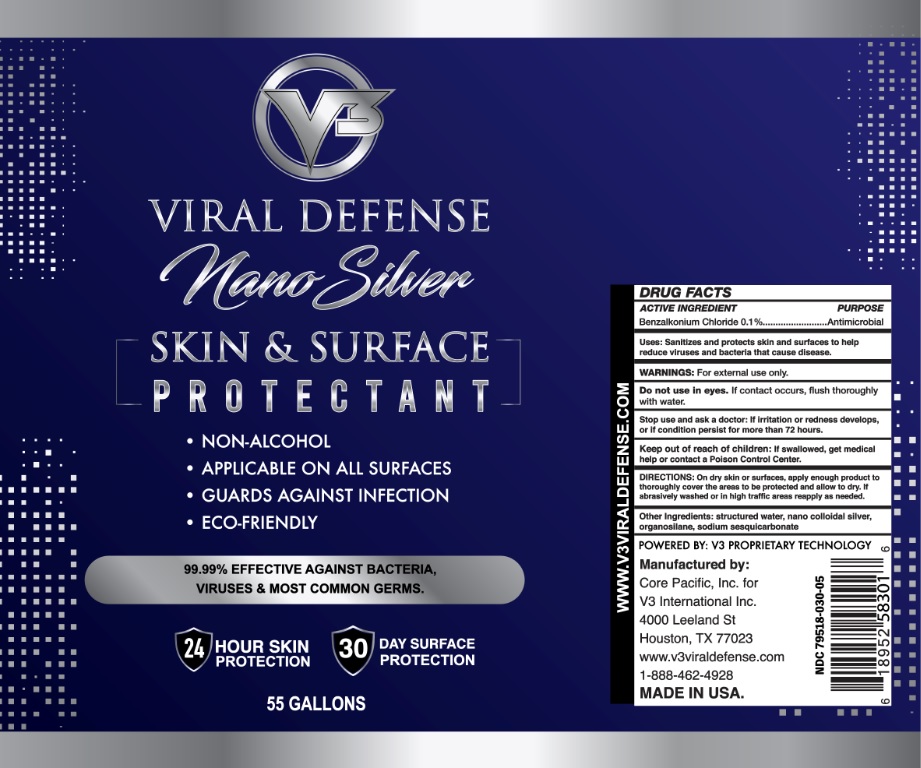 DRUG LABEL: V3 Viral Defense Nano Silver Skin and Surface Protectant
NDC: 79518-030 | Form: LIQUID
Manufacturer: Core Pacific, Inc.
Category: otc | Type: HUMAN OTC DRUG LABEL
Date: 20200810

ACTIVE INGREDIENTS: BENZALKONIUM CHLORIDE 0.1 g/100 mL
INACTIVE INGREDIENTS: WATER; SILVER; .GAMMA.-METHACRYLOXYPROPYLTRIMETHOXYSILANE; SODIUM SESQUICARBONATE

V3 VIRAL DEFENSE nano Silver SKIN & SURFACE PROTECTANT

ACTIVE INGREDIENT

Benzalkonium Chloride 0.1%

PURPOSE

Antimicrobial

INDICATIONS AND USAGE

Uses: Sanitizes and protects skin and surface to help reduce viruses and bacteria that cause disease.

WARNINGS:

For external use only.

Do not use in eyes. If contact occurs, flush thoroughly with water.

Stop use and ask a doctor: if irritation or redness develops, or if condition persist for more than 72 hours.

Keep out of reach of children: If swallowed, get medical help or contact a Poison Control Center.

DOSAGE AND ADMINISTRATION

DIRECTIONS: On dry skin or surfaces, apply enough product to thoroughly cover the areas to be protected and allow to dry. If abrasively washed or in high traffic areas reapply as needed.

INACTIVE INGREDIENT

Other Ingredients: structured water, nano colloidal silver, organosilane, sodium sesquicarbonate

• NON-ALCOHOL

• APPLICABLE ON ALL SURFACES

• GUARDS AGAINST INFECTION

• ECO-FRIENDLY

99.99% EFFECTIVE AGAINST BACTERIA, VIRUSES & MOST COMMON GERMS.

24 HOURS SKIN PROTECTION

30 DAY SURFACE PROTECTION

POWERED BY: V3 PROPRIETARY TECHNOLOGY

Manufactured by:

Core Pacific, Inc. for

V3 International Inc.

4000 Leeland St

Houston, TX 77023

www.v3viraldefense.com

1-888-462-4928

MADE IN USA.